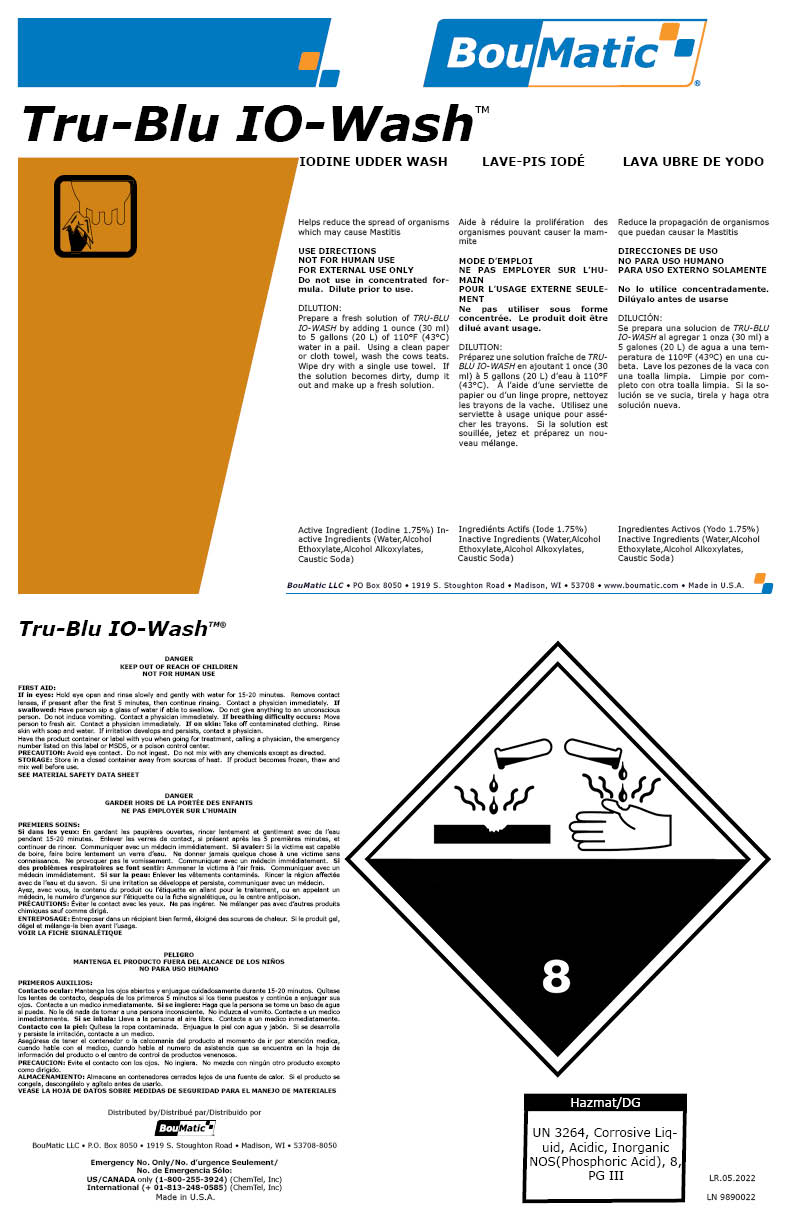 DRUG LABEL: Tru-Blu IO-Wash
NDC: 48106-2057 | Form: LIQUID
Manufacturer: BOUMATIC, LLC
Category: animal | Type: OTC ANIMAL DRUG LABEL
Date: 20241002

ACTIVE INGREDIENTS: IODINE .018 kg/100 kg

Tru-Blu IO-Wash

Claim of effectiveness.

Helps reduce the spread of organisms
which may cause Mastitis

Use Directions

NOT FOR HUMAN USE
FOR EXTERNAL USE ONLY
Do not use in concentrated formula.
Dilute prior to use.
DILUTION:
Prepare a fresh solution of TRU-BLU
IO-WASH by adding 1 ounce (30 ml)
to 5 gallons (20 L) of 110°F (43°C)
water in a pail. Using a clean paper
or cloth towel, wash the cows teats.
Wipe dry with a single use towel. If
the solution becomes dirty, dump it
out and make up a fresh solution.

First Aid

If in eyes: Hold eye open and rinse slowly and gently with water for 15-20 minutes. Remove contact
lenses, if present after the first 5 minutes, then continue rinsing. Contact a physician immediately. If
swallowed: Have person sip a glass of water if able to swallow. Do not give anything to an unconscious
person. Do not induce vomiting. Contact a physician immediately. If breathing difficulty occurs: Move
person to fresh air. Contact a physician immediately. If on skin: Take off contaminated clothing. Rinse
skin with soap and water. If irritation develops and persists, contact a physician.
Have the product container or label with you when going for treatment, calling a physician, the emergency
number listed on this label or MSDS, or a poison control center.

PRECAUTION:

Avoid eye contact. Do not ingest. Do not mix with any chemicals except as directed.

STORAGE:

Store in a closed container away from sources of heat. If product becomes frozen, thaw and
mix well before use.